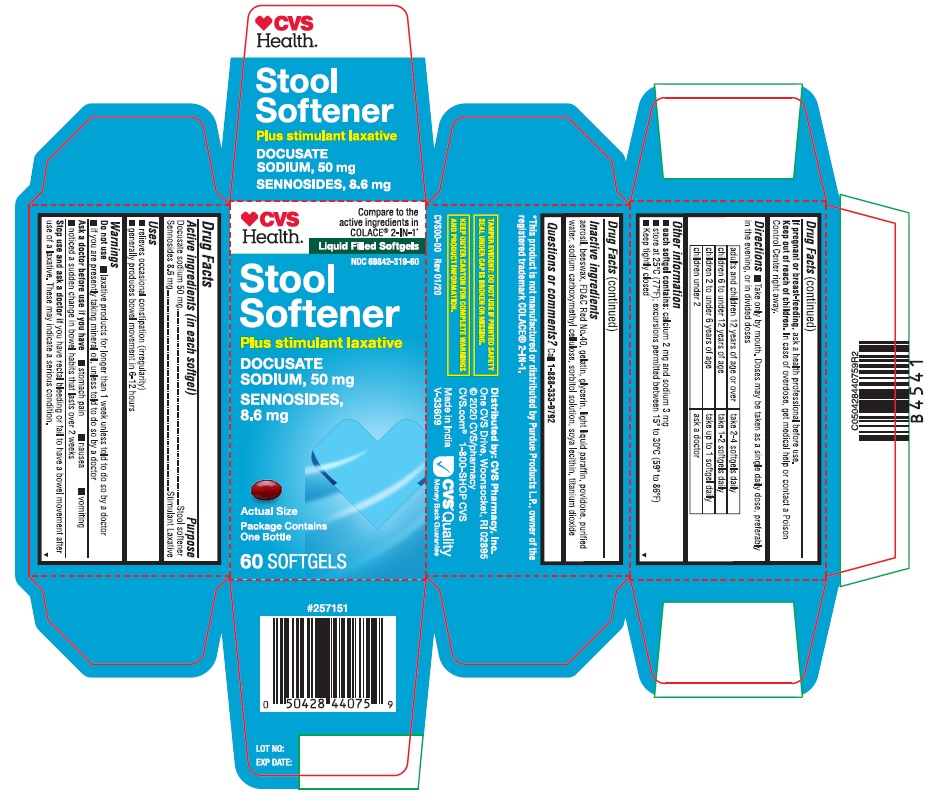 DRUG LABEL: STOOL SOFTENER
NDC: 69842-319 | Form: CAPSULE, GELATIN COATED
Manufacturer: CVS
Category: otc | Type: HUMAN OTC DRUG LABEL
Date: 20241217

ACTIVE INGREDIENTS: DOCUSATE SODIUM 50 mg/1 1; SENNOSIDES 8.6 mg/1 1
INACTIVE INGREDIENTS: SILICON DIOXIDE; YELLOW WAX; FD&C RED NO. 40; GELATIN; GLYCERIN; LIGHT MINERAL OIL; POVIDONE K30; WATER; CARBOXYMETHYLCELLULOSE SODIUM; SORBITOL; LECITHIN, SOYBEAN; TITANIUM DIOXIDE

STOOL SOFTENER

DRUG FACTS

Active ingredients (in each softgel) | Purpose
Docusate sodium 50 mg | Stool softener
Sennosides 8.6 mg | Stimulant Laxative

Uses

- relieves occasional constipation (irregularity)
- generally produces bowel movement in 6-12 hours

Warnings

Do not use

- laxative products for longer than 1 week unless told to do so by a doctor
- if you are presently taking mineral oil, unless told to do so by a doctor

Ask a doctor before use if you have

- stomach pain
- nausea
- vomiting
- noticed a sudden change in bowel habits that lasts over 2 weeks

Stop use and ask a doctor if you have rectal bleeding or fail to have a bowel movement after use of a laxative. These may indicate a serious condition.

PREGNANCY OR BREAST FEEDING

If pregnant or breast-feeding, ask a health professional before use.

Keep out of reach of children. In case of overdose, get medical help or contact a Poison Control Center right away.

Directions

- Take only by mouth. Doses may be taken as a single daily dose, preferably in the evening, or in divided doses

adults and children 12 years of age or over | take 2-4 softgels daily
children 6 to under 12 years of age | take 1-2 softgels daily
children 2 to under 6 years of age | take upto 1 softgel daily
children under 2 | ask a doctor

Other information

- each softgel contains: calcium 2 mg and sodium 3 mg
- store at 25°C (77°F); excursions permitted between 15°-30°C (59°-86°F)
- Keep tightly closed

Inactive ingredients

Aerosil, beeswax, FD&C Red No.40, gelatin, glycerin, light liquid paraffin, povidone (PVP K-30), purified water, sodium carboxymethylcellulose, sorbitol solution, soya lecithin, titanium dioxide

Questions?

Call 1-888-333-9792 Monday-Friday 9AM-5PM EST

Distributed by: CVS Pharmacy, Inc.
One CVS Drive, Woonsocket, RI 02895

PRINCIPAL DISPLAY PANEL

♥CVSHealth™

Compare to the
active ingredients in
COLACE® 2-IN-1*

Liquid Filled Softgels

NDC 69842-319-60

Stool Softener
DOCUSATE SODIUM, 50 mg
SENNOSIDES, 8.6 mg
Plus stimulant laxative

Package Contains One Bottle

60 SOFTGELS

Actual Size

*This product is not manufactured or distributed by Purdue Products L.P., owner of the
registered trademark COLACE® 2-IN-1.